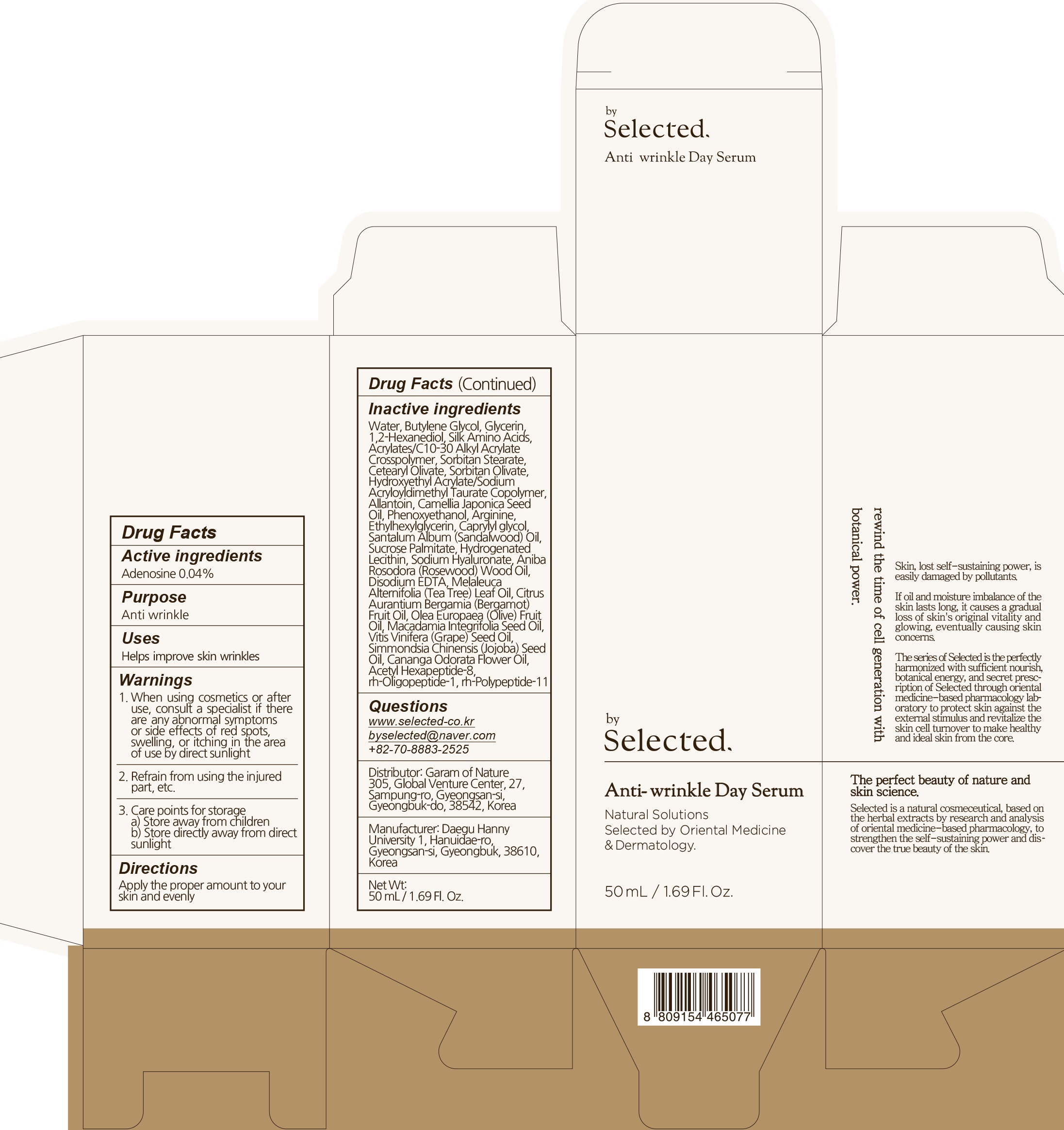 DRUG LABEL: by selected anti wrinkle day serum
NDC: 73509-020 | Form: LIQUID
Manufacturer: Garam Of Nature
Category: otc | Type: HUMAN OTC DRUG LABEL
Date: 20191217

ACTIVE INGREDIENTS: Adenosine 0.02 g/50 mL
INACTIVE INGREDIENTS: Water; Butylene Glycol

ACTIVE INGREDIENT

Active ingredients: Adenosine 0.04%

INACTIVE INGREDIENT

Inactive ingredients:

Water, Butylene Glycol, Glycerin, 1,2-Hexanediol, Silk Amino Acids, Acrylates/C10-30 Alkyl Acrylate Crosspolymer, Sorbitan Stearate, Cetearyl Olivate, Sorbitan Olivate, Hydroxyethyl Acrylate/Sodium Acryloyldimethyl Taurate Copolymer, Allantoin, Camellia Japonica Seed Oil, Phenoxyethanol, Arginine, Ethylhexylglycerin, Caprylyl glycol, Santalum Album, Sucrose Palmitate, Hydrogenated Lecithin, Sodium Hyaluronate, Aniba Rosodora, Disodium EDTA, Melaleuca Alternifolia (Tea Tree) Leaf Oil, Citrus Aurantium Bergamia (Bergamot) Fruit Oil, Olea Europaea (Olive) Fruit Oil, Macadamia Integrifolia Seed Oil, Vitis Vinifera (Grape) Seed Oil, Simmondsia Chinensis (Jojoba) Seed Oil, Cananga Odorata Flower Oil, Acetyl Hexapeptide-8, rh-Oligopeptide-1, rh-Polypeptide-11

PURPOSE

Purpose: Anti wrinkle

WARNINGS

1. In case of having following symptoms after using this, you're advised to stop using it immediately. If you keep using it, the symptoms will get worse and need to consult a dermatologist 1) In case of having problems such as red rash, swollenness, itching, stimulation during usage 2) In case of having the same symptoms above on the part you put this product on by direct sunlight 2. You are banned to use it on the part where you have a scar, eczema, or dermatitis 3. In case of getting it into your eyes, you have to wash it immediately 4. Caution for treatment and keeping 1) Tighten the lid after using it 2) Keep it out of infants or children's reach 3) Don't keep it in the place where the temperature is extremely hot or low and exposed to the direct sunlight

KEEP OUT OF REACH OF CHILDREN

Keep it out of infants or children's reach

Uses

Helps improve skin wrinkles

Directions

Apply the proper amount to your skin and evenly

QUESTIONS

www.selected-co.kr
byselected@naver.com
+82-70-8883-2525